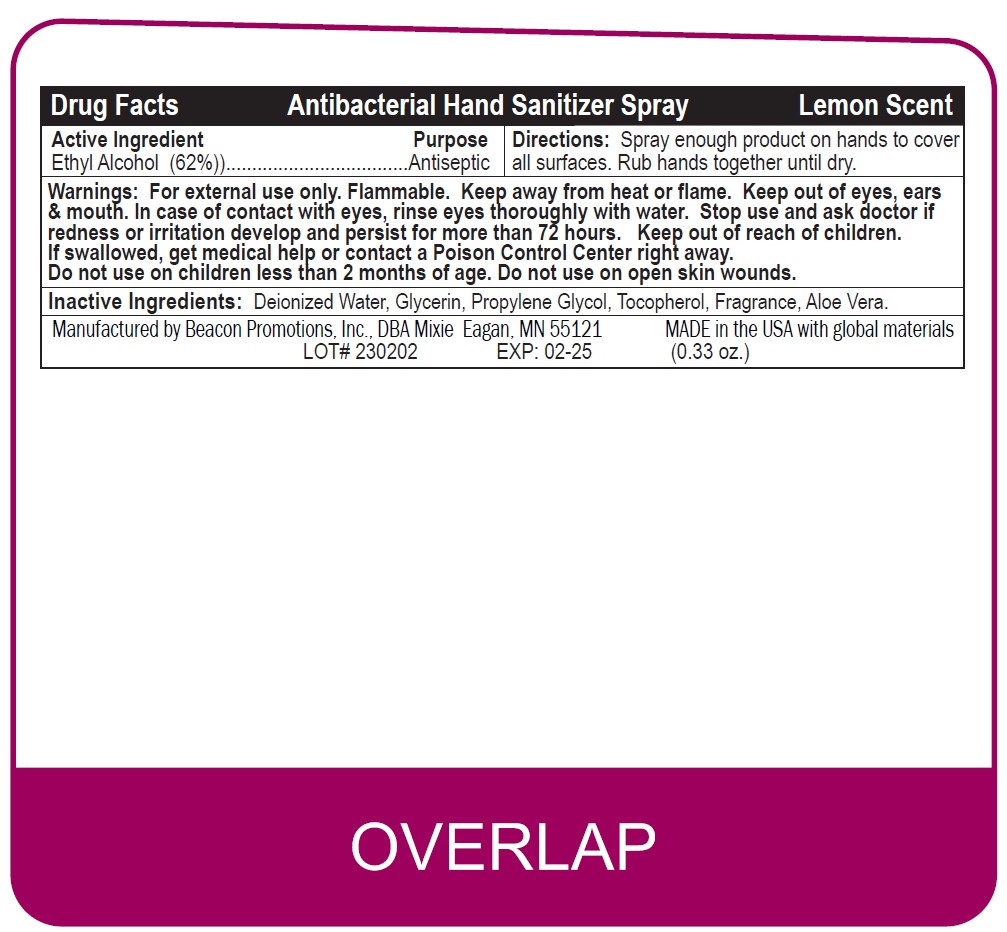 DRUG LABEL: SANSPRAY
NDC: 70445-605 | Form: SPRAY
Manufacturer: Beacon Promotions Inc
Category: otc | Type: HUMAN OTC DRUG LABEL
Date: 20250428

ACTIVE INGREDIENTS: ALCOHOL 62 mL/100 mL
INACTIVE INGREDIENTS: .ALPHA.-TOCOPHEROL ACETATE; PROPYLENE GLYCOL; ALOE; GLYCERIN

Alcohol Sanitizer Spray

Drug facts

Ethyl Alcohol (62%)

DOSAGE AND ADMINISTRATION

Ethyl Alcohol (62%)

Spray enough product on hands to cover
all surfaces. Rub hands together until dry.

Inactive ingredients

Deionized Water, Glycerin, Propylene Glycol, Tocopherol, Fragrance, Aloe Vera.

Purpose

Antiseptic

Purpose

Anticeptic

Directions

Spray enough product on hands to cover
all surfaces. Rub hands together until dry.

Warnings

For external use only. Flammable. Keep away from heat or flame. Keep out of eyes, ears
& mouth. In case of contact with eyes, rinse eyes thoroughly with water. Stop use and ask doctor if
redness or irritation develop and persist for more than 72 hours. Keep out of reach of children.
If swallowed, get medical help or contact a Poison Control Center right away.
Do not use on children less than 2 months of age. Do not use on open skin wounds.

Keep out of reach of children